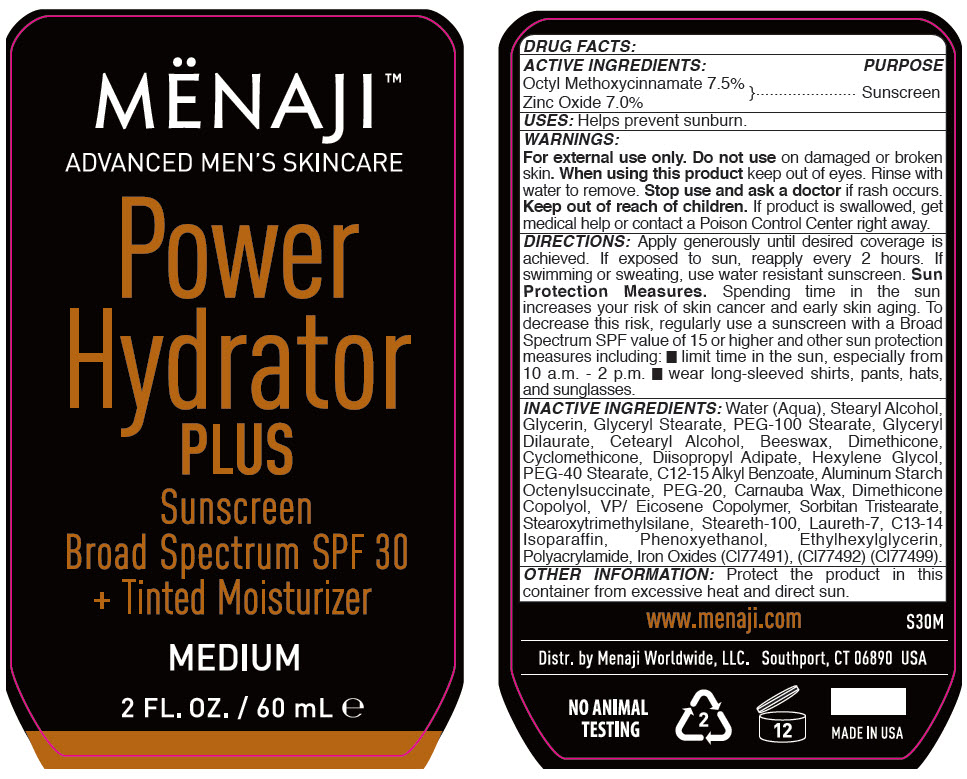 DRUG LABEL: Menaji Power Hydrator Plus Sunscreen Broad Spectrum SPF 30 Plus Tinted Moisturize Medium
NDC: 66163-7621 | Form: CREAM
Manufacturer: Cosmetic Solutions LLC
Category: otc | Type: HUMAN OTC DRUG LABEL
Date: 20191001

ACTIVE INGREDIENTS: Octinoxate 75 mg/1 mL; Zinc Oxide 70 mg/1 mL
INACTIVE INGREDIENTS: Water; Stearyl Alcohol; Glycerin; Glyceryl Monostearate; PEG-100 Stearate; Glyceryl Dilaurate; Cetostearyl Alcohol; Yellow Wax; Dimethicone; Cyclomethicone; Diisopropyl Adipate; Hexylene Glycol; PEG-40 Stearate; Alkyl (C12-15) Benzoate; Aluminum Starch Octenylsuccinate; POLYETHYLENE GLYCOL 1000; Carnauba Wax; PEG/PPG-18/18 Dimethicone; Sorbitan Tristearate; Stearoxytrimethylsilane; Steareth-100; Laureth-7; C13-14 Isoparaffin; Phenoxyethanol; Ethylhexylglycerin; Ferric Oxide Red; Ferric Oxide Yellow; Ferrosoferric Oxide

Mënaji™ – Power Hydrator Plus Sunscreen Broad Spectrum SPF 30 + Tinted Moisturize Medium

DRUG FACTS:

ACTIVE INGREDIENTS

Octyl Methoxycinnamate 7.5%

Zinc Oxide 7.0%

PURPOSE

Sunscreen

USES

Helps prevent sunburn.

WARNINGS

For external use only. Do not use on damaged or broken skin. When using this product keep out of eyes. Rinse with water to remove. Stop use and ask a doctor if rash occurs.

Keep out of reach of children. If product is swallowed, get medical help or contact a Poison Control Center right away.

DIRECTIONS

Apply generously until desired coverage is achieved. If exposed to sun, reapply every 2 hours. If swimming or sweating, use water resistant sunscreen. Sun Protection Measures. Spending time in the sun increases your risk of skin cancer and early skin aging. To decrease this risk, regularly use a sunscreen with a Broad Spectrum SPF value of 15 or higher and other sun protection measures including:

- limit time in the sun, especially from 10 a.m. - 2 p.m.
- wear long-sleeved shirts, pants, hats, and sunglasses.

INACTIVE INGREDIENTS

Water (Aqua), Stearyl Alcohol, Glycerin, Glyceryl Stearate, PEG-100 Stearate, Glyceryl Dilaurate, Cetearyl Alcohol, Beeswax, Dimethicone, Cyclomethicone, Diisopropyl Adipate, Hexylene Glycol, PEG-40 Stearate, C12-15 Alkyl Benzoate, Aluminum Starch Octenylsuccinate, PEG-20, Carnauba Wax, Dimethicone Copolyol, VP/ Eicosene Copolymer, Sorbitan Tristearate, Stearoxytrimethylsilane, Steareth-100, Laureth-7, C13-14 Isoparaffin, Phenoxyethanol, Ethylhexylglycerin, Polyacrylamide, Iron Oxides (CI77491), (CI77492) (CI77499).

OTHER INFORMATION

Protect the product in this container from excessive heat and direct sun.

Distr. by Manaji Worldwide, LLC. Southport, CT 06890 USA

PRINCIPAL DISPLAY PANEL - 60 mL Bottle Label

MËNAJI™
ADVANCED MEN'S SKINCARE

Power
Hydrator
PLUS

Sunscreen
Broad Spectrum SPF 30
+ Tinted Moisturizer

MEDIUM

2 FL. OZ. / 60 mL e